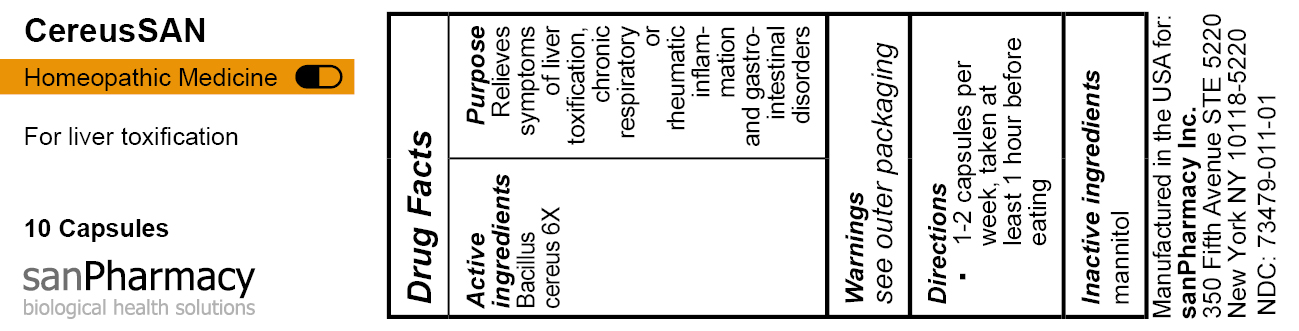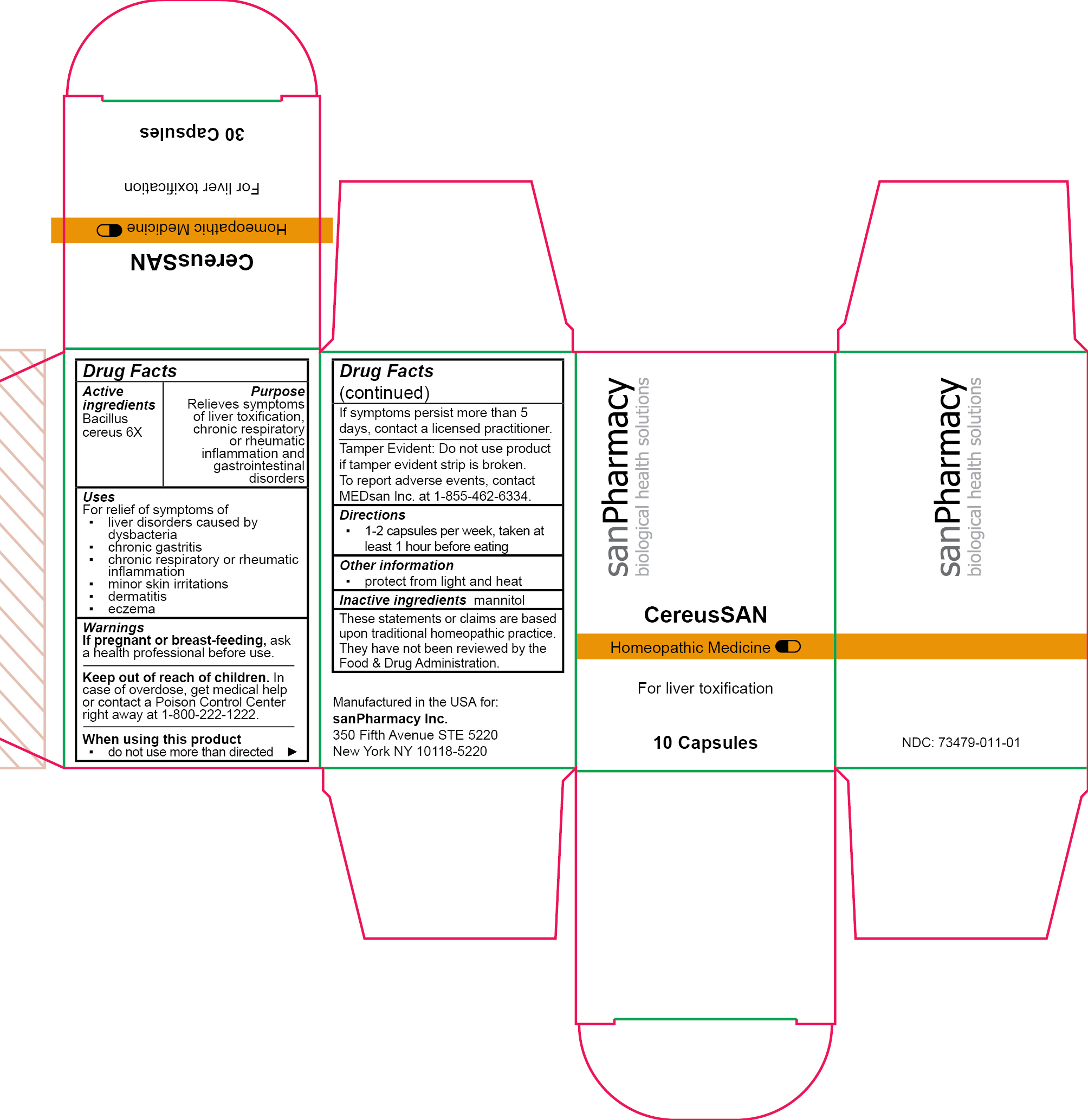 DRUG LABEL: CereusSAN
NDC: 73479-011 | Form: CAPSULE
Manufacturer: sanPharmacy Inc.
Category: homeopathic | Type: HUMAN OTC DRUG LABEL
Date: 20240423

ACTIVE INGREDIENTS: BACILLUS CEREUS 6 [hp_X]/1 1
INACTIVE INGREDIENTS: MANNITOL

CereusSAN Capsules

INDICATIONS AND USAGE

For liver toxification

PURPOSE

Relieves symptoms of liver toxification, chronic respiratory or rheumatic inflammation and gastrointestinal disorders

ACTIVE INGREDIENT

Bacillus cereus 6X

INACTIVE INGREDIENT

Mannitol

DOSAGE AND ADMINISTRATION

1-2 capsules per week, taken at least 1 hour before eating

WARNINGS

If pregnant or breast-feeding, ask a health professional before use.
______________________________
Keep out of reach of children. In case of overdose, get medical help or contact a Poison Control Center right away at 1-800-222-1222.
______________________________
When using this product
▪ do not use more than directed
______________________________
If symptoms persist more than 5 days, contact a licensed practitioner.
______________________________
Tamper Evident: Do not use product if tamper evident strip is broken. To report adverse events, contact MEDsan Inc. at 1-855-462-6334.

Keep out of reach of children. In case of overdose, get medical help or contact a Poison Control Center right away at 1-800-222-1222

STORAGE AND HANDLING

Tamper Evident: Do not use product if tamper evident strip is broken. To report adverse events, contact MEDsan Inc. at 1-855-462-6334

Manufactured in the USA for:
sanPharmacy Inc.
350 Fifth Avenue STE 5220
New York NY 10118-5220

Liability statement

These statements or claims are based upon traditional homeopathic practice. They have not been reviewed by the Food & Drug Administration

STORAGE AND HANDLING

protect from light and heat

PACKAGE LABEL

CereusSAN

Homeopathic Medicine

For liver toxification

10 Capsules

sanPharmacy

biological health solutions